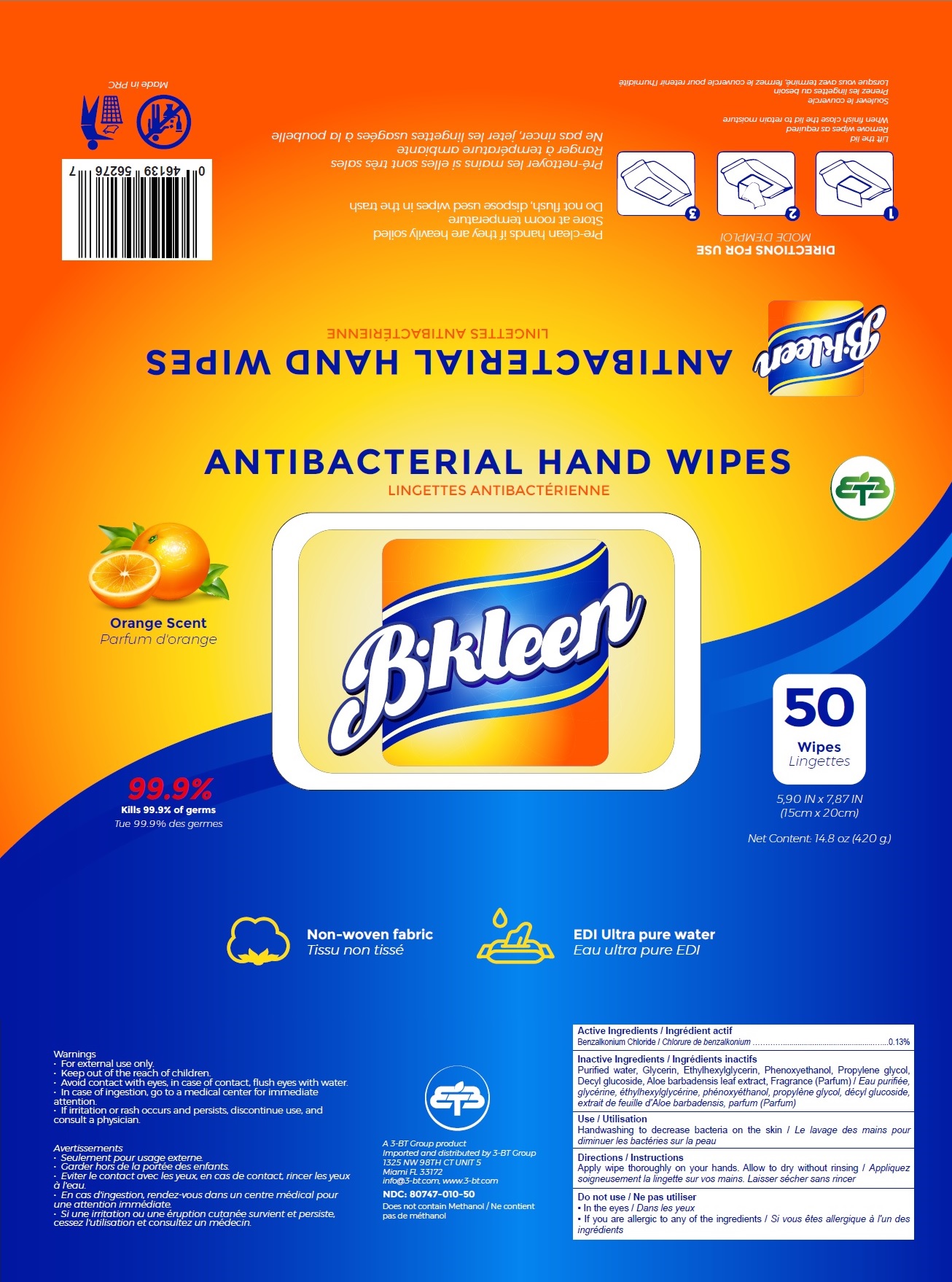 DRUG LABEL: B-Kleen Antibacterial Hand Wipes
NDC: 80747-010 | Form: CLOTH
Manufacturer: 3-BT Group, LLC
Category: otc | Type: HUMAN OTC DRUG LABEL
Date: 20201008

ACTIVE INGREDIENTS: BENZALKONIUM CHLORIDE 0.13 g/100 mL
INACTIVE INGREDIENTS: WATER; GLYCERIN; ETHYLHEXYLGLYCERIN; PHENOXYETHANOL; PROPYLENE GLYCOL; DECYL GLUCOSIDE; ALOE VERA LEAF

B.kleen ANTIBACTERIAL HAND WIPES

Active Ingredients

Benzalkonium Chloride......................0.13%

Purpose

Antiseptic

Inactive Ingredients

Purified water, Glycerin, Ethylhexylglycerin, Phenoxyethanol, Propylene glycol, Decyl glucoside, Aloe barbadensis leaf extract, Fragrance (Parfum)

Use

Handwashing to decrease bacteria on the skin

Directions

Apply wipe thoroughly on your hands. Allow to dry without rinsing

Do not use
• In the eyes
• If you are allergic to any of the ingredients

Warnings
• For external use only.
• Avoid contact with eyes, in case of contact, flush eyes with water.
• In case of ingestion, go to a medical center for immediate attention.
• If irritation or rash occurs and persists, discontinue use, and consult a physician.

• Keep out of the reach of children.

Non-woven fabric

EDI Ultra pure water

99.9%

Kills 99.9% of germs

Orange Scent

DIRECTIONS FOR USE

Lift the lid
Remove wipes as required
When finish close the lid to retain moisture

Pre-clean hands if they are heavily soiled
Store at room temperature
Do not flush, dispose used wipes in the trash

Made in PRC

A 3-BT Group product
Imported and distributed by 3-BT Group
1325 NW 98TH CT UNIT 5
Miami FL 33172
info@3-bt.com, www.3-bt.com

Does not contain Methanol